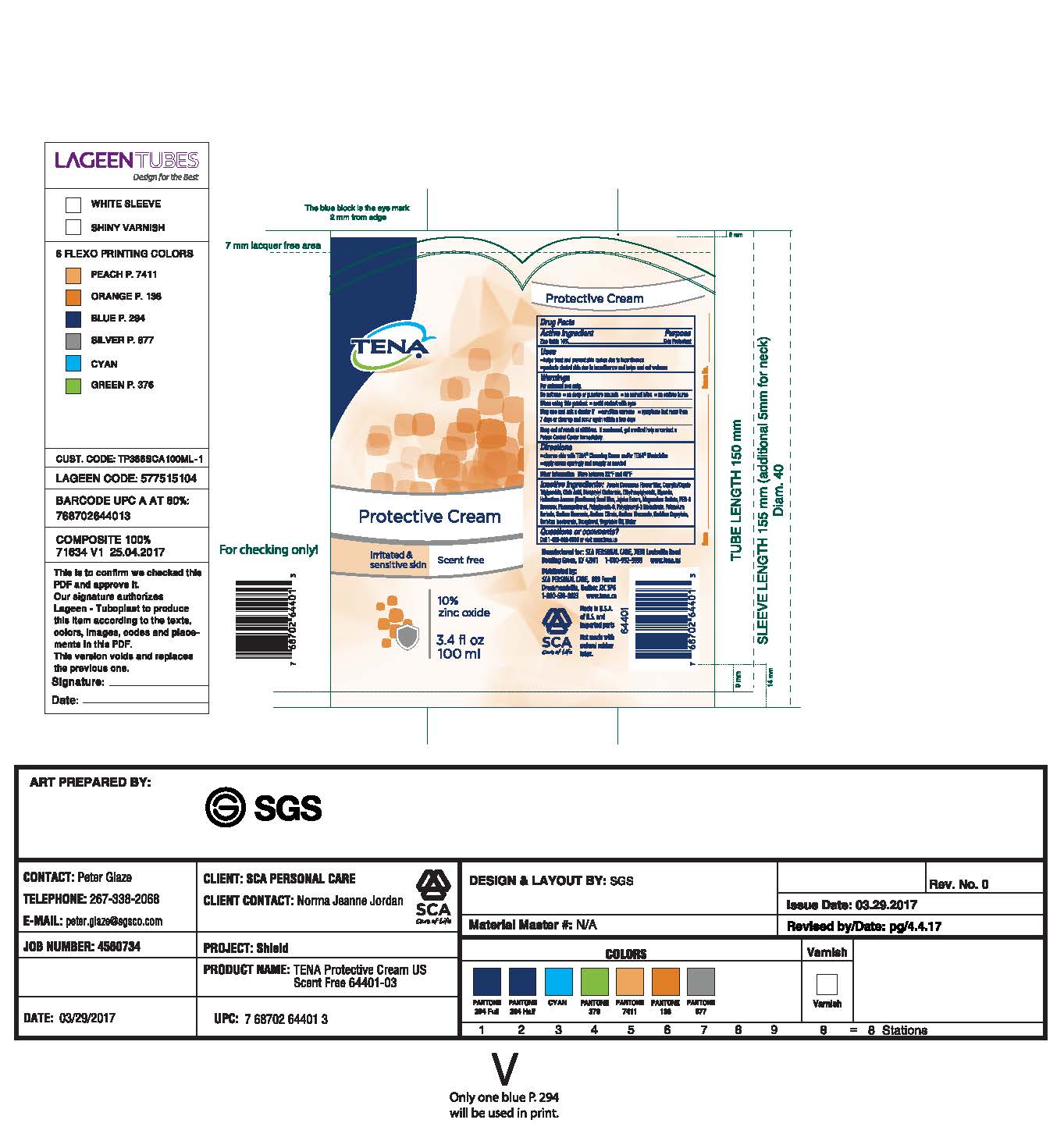 DRUG LABEL: TENA
NDC: 59608-003 | Form: LOTION
Manufacturer: SCA Personal Care Inc.
Category: otc | Type: HUMAN OTC DRUG LABEL
Date: 20170718

ACTIVE INGREDIENTS: ZINC OXIDE 10 g/100 mL
INACTIVE INGREDIENTS: ACACIA DECURRENS FLOWER WAX; MEDIUM-CHAIN TRIGLYCERIDES; CITRIC ACID MONOHYDRATE; DICAPRYLYL CARBONATE; ETHYLHEXYLGLYCERIN; GLYCERIN; HELIANTHUS ANNUUS SEED WAX; HYDROGENATED JOJOBA OIL, RANDOMIZED; MAGNESIUM SULFATE, UNSPECIFIED FORM; YELLOW WAX; PHENOXYETHANOL; POLYGLYCERIN-3; POLYGLYCERYL-3 RICINOLEATE; POTASSIUM SORBATE; SODIUM BENZOATE; SODIUM CITRATE; SODIUM GLUCONATE; SORBITAN; SORBITAN ISOSTEARATE; TOCOPHEROL; CORN OIL; WATER

Active Ingredient

Zinc Oxide 10%

Purpose

Skin Protectant

Uses

•helps treat and prevent skin rashes due to incontinence

•protects chafed skin due to incontinence and helps seal out wetness

Warnings

For external use only.

Do not use •on deep or puncture wounds •on animal bites •on serious burns

When using this product •avoid contact with eyes

Stop use and ask a doctor if •condition worsens •symptoms last more than

7 days or clear up and occur again within a few days

Keep out of reach of children. If swallowed, get medical help or contact a

Poison Control Center immediately

Directions

•cleanse skin with TENA® Cleansing Cream and/or TENA® Washcloths

•apply cream sparingly and reapply as needed

Other information Store between 32° F and 85° F

INACTIVE INGREDIENT

Inactive ingredients: Acacia Decurrens Flower Wax, Caprylic/Capric Triglyceride, Citric Acid, Dicaprylyl Carbonate,

Ethylhexylglycerin, Glycerin, Helianthus Annuus (Sunflower) Seed Wax, Jojoba Esters, Magnesium Sulfate, PEG-8 Beeswax, Polyglycerin-3,

Polyglyceryl-3 Ricinoleate, Potassium Sorbate, Sodium Benzoate, Sodium Citrate, Sodium Gluconate, Sorbitan Caprylate, Sorbitan

Isostearate, Tocopherol, Vegetable Oil, Water.